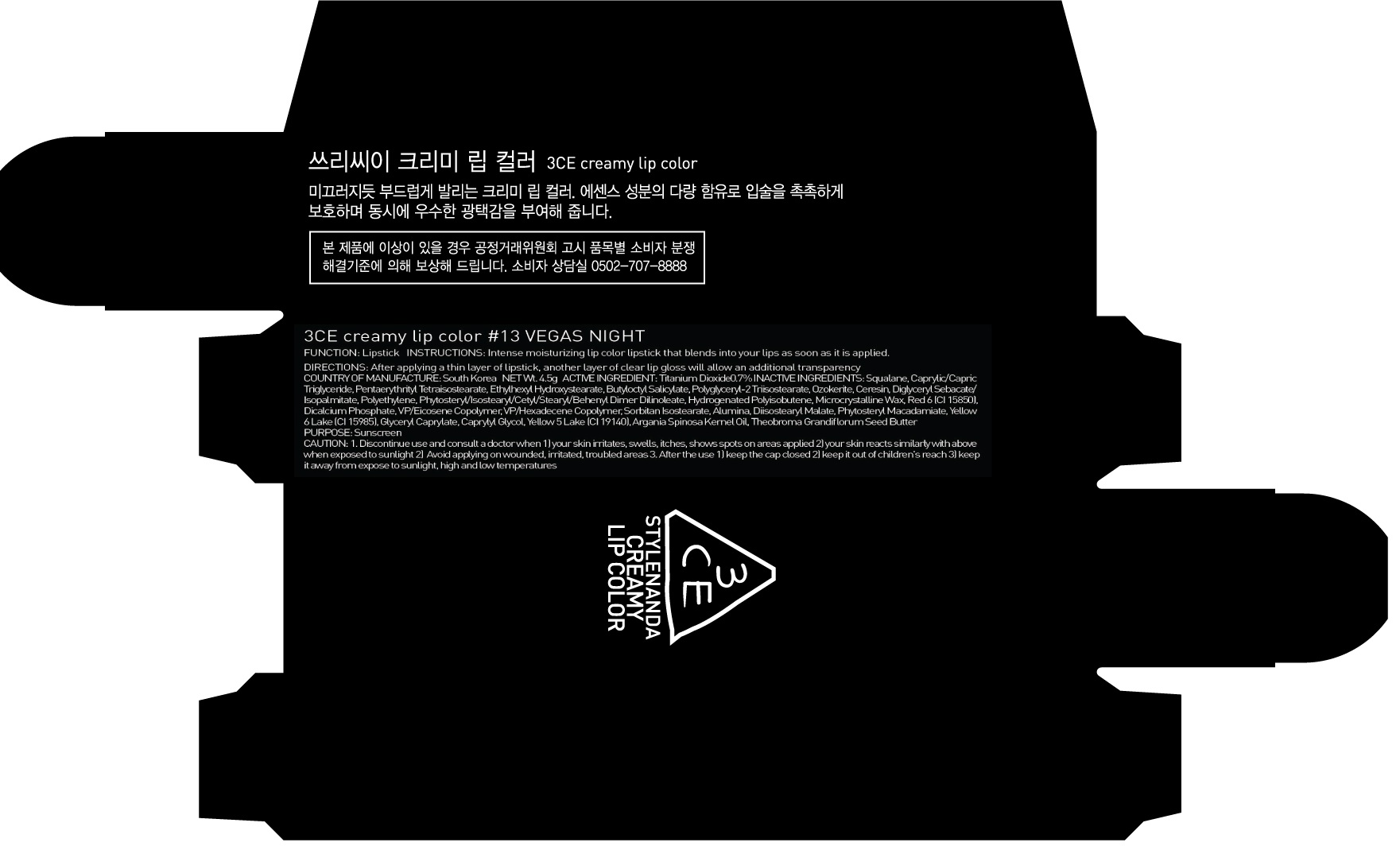 DRUG LABEL: 3CE CRE AMY LIP COLOR 13 VEG AS NIGHT
NDC: 60764-121 | Form: LIPSTICK
Manufacturer: Nanda Co., Ltd
Category: otc | Type: HUMAN OTC DRUG LABEL
Date: 20161014

ACTIVE INGREDIENTS: Titanium Dioxide 0.03 g/4.5 g
INACTIVE INGREDIENTS: Squalane; Pentaerythrityl Tetraisostearate

ACTIVE INGREDIENT

Active Ingredient: Titanium Dioxide 0.7%

INACTIVE INGREDIENT

Inactive Ingredients: Squalane, Caprylic/Capric Triglyceride, Pentaerythrityl Tetraisostearate, Ethylhexyl Hydroxystearate, Butyloctyl Salicylate, Polyglyceryl-2 Triisostearate, Ozokerite, Ceresin, Diglyceryl Sebacate/Isopalmitate, Polyethylene, Phytosteryl/Isostearyl/Cetyl/Stearyl/Behenyl Dimer Dilinoleate, Hydrogenated Polyisobutene, Microcrystalline Wax, Red 6 (CI 15850), Dicalcium Phosphate, VP/Eicosene Copolymer, VP/Hexadecene Copolymer, Sorbitan Isostearate, Alumina, Diisostearyl Malate, Phytosteryl Macadamiate, Yellow 6 Lake (CI 15985), Glyceryl Caprylate, Caprylyl Glycol, Yellow 5 Lake (CI 19140), Argania Spinosa Kernel Oil, Theobroma Grandiflorum Seed Butter

PURPOSE

Purpose: Sunscreen

CAUTION

CAUTION: 1. Discontinue use and consult a doctor when - your skin irritates, swells, itches, shows spots on areas applied - your skin reacts similarly with above when exposed to sunlight 2. Avoid applying on wounded, irritated, troubled areas 3. After the use - keep the cap closed - keep it out of children's reach - keep it away from expose to sunlight, high and low temperatures

DESCRIPTION

INSTRUCTIONS: Intense moisturizing lip color lipstick that blends into your lips as soon as it is applied.

Directions: After applying a thin layer of lipstick, another layer of clear lip gloss will allow an additional transparency